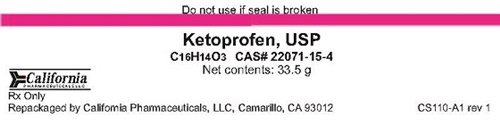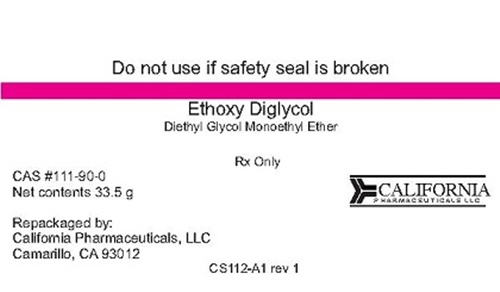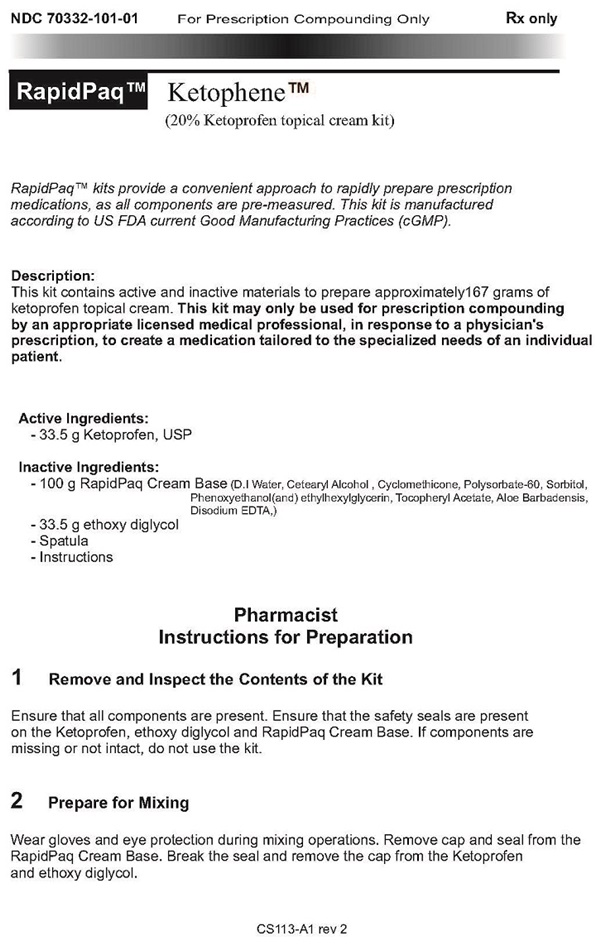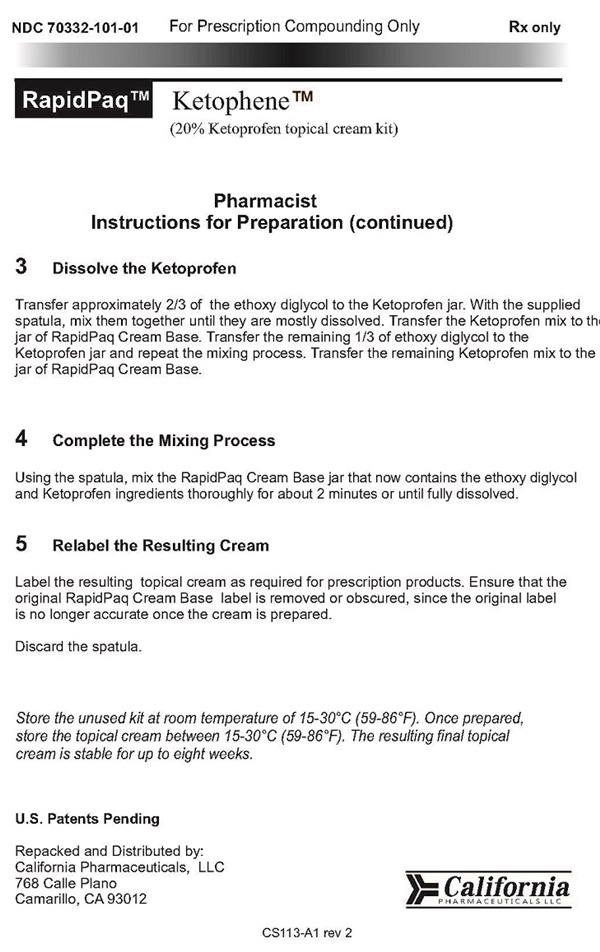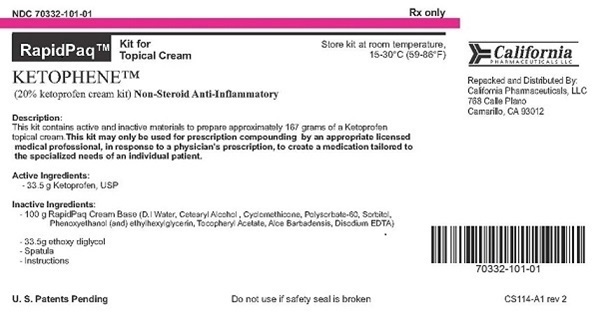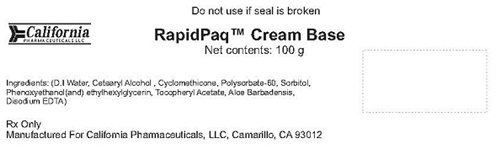 DRUG LABEL: KETOPHENE
NDC: 70332-101 | Form: KIT | Route: TOPICAL
Manufacturer: California Pharmaceuticals, LLC
Category: prescription | Type: HUMAN PRESCRIPTION DRUG LABEL
Date: 20160721

ACTIVE INGREDIENTS: KETOPROFEN 33.5 g/33.5 g
INACTIVE INGREDIENTS: DIETHYLENE GLYCOL MONOETHYL ETHER; WATER; CETOSTEARYL ALCOHOL; CYCLOMETHICONE; POLYSORBATE 60; SORBITOL; PHENOXYETHANOL; ETHYLHEXYLGLYCERIN; .ALPHA.-TOCOPHEROL ACETATE; ALOE VERA LEAF; EDETATE SODIUM

KETOPHENE - 70332-101

Instructions for Preparation Page 1 Page 2

NDC 70332-101-01 For Prescription Compounding Only Rx only

RapidPaq™ Ketophene™

(20% Ketoprofen topical cream kit)

RapidPaq™ kits provide a convenient approach to rapidly prepare prescription medications, as all components are pre-measured. This kit is manufactured according to US FDA current Good Manufacturing Practices (cGMP).

Description:

This kit contains active and inactive materials to prepare approximately 167 grams of ketoprofen topical cream. This kit may only be used for prescription compounding by an appropriate licensed medical professional, in response to a physician's prescription, to create a medication tailored to the specialized needs of an individual patient.

Active Ingredients:

- 33.5 g Ketoprofen, USP

Inactive Ingredients:

- 100 g RapidPaq Cream Base (D.I Water, Cetearyl Alcohol, Cyclomethicone, Polysorbate-60, Sorbitol, Phenoxyethanol(and)ethylhexlglycerin,

Tocopheryl Acetate, Aloe Barbadensis, Disodium EDTA,)

- 33.5 g ethoxy diglycol

- Spatula

-Instructions

Pharmacist instructions for Preparation

1 Remove and Inspect the Contents of the Kit

Ensure that all components are present. Ensure that the safety seals are present on the Ketoprofen, ethoxy diglycol and RapidPaq Cream Base. If components are missing or not intact, do not use the kit.

2 Prepare for Mixing

Wear gloves and eye protection during mixing operations. Remove cap and seal from the RapidPaq Cream Base. Break the seal and remove the cap from the Ketoprofen and ethoxy diglycol.

3 Dissole the Ketoprofen

Transfer approximately 2/3 of the ethoxy diglycol to the Ketoprofen jar. With the supplied spatula, mix them together until they are mostly dissolved. Transfer the Ketoprofen mix to the jar of RapidPaq Cream Base. Transfer the remaining 1/3 of ethoxy diglycol to the Ketoprofen jar and repeat the mixing process. transfer the remaining Ketoprofen mix to the jar of RapidPaq Cream Base.

4 Complete the Mixing Process

Using the spatula, mix the RapidPaq Crean base jar that now contains the ethoxy diglycol and Ketoprofrn ingredients thoroughly for about 2 minutes or until fully dissolved.

5 Relabel the Resulting Cream

Label the resulting topical cream as required for prescription products. Ensure that the original RapidPaq Cream Base label is removed or obscured, since the original label is no longer accurate once the cream is prepared.

Discard the spatula.

Store the unused kit at room temperature of 15-30°C (59-86°F). Once prepared, store the topical cream between 15-30°C (59-86°F). The resulting final topical cream is stable for up to eight weeks.

U.S. Patents Pending

Repacked and Distributed by:

California Pharmaceuticals, LLC

768 Calle Plano

Camarillo, CA 93012

CS113-A1 rev 2

California

PHARMACEUTICALS LLC

RapidPaq™ Cream Base product label

Do not use if seal is broken

California

PHARMACEUTICALS LLC

RapidPaq™ Cream Base

Net contents: 100g

Ingredients: (D.I Water, Cetearyl Alcohol, Cyclomethicone, Polysorbate-60, Sorbitol, Phenoxyethanol(and)ethylhexlglycerin, Tocopheryl Acetate, Aloe Barbadensis, Disodium EDTA

RX Only

Manufactured For California Pharmaceuticals, LLC, Camarillo, CA 93012

Ethoxy Diglycol product label

Do not use if safety seal is broken

Ethoxy Diglycol

Diethyl Glycol Monoethly Ether

CAS # 111-90-0

Net contents 33.5 g

Rx Only

Repackaged By;

California Pharmaceuticals, LLC

Camarillo, Ca 93012

California

PHARMACEUTICALS LLC

cs112-A1 rev 1

Ketoprofen, USP product label

Do not use if seal is broken

Ketoprofen, USP

C16H14O3 CAS # 22071-15-4

Net contents: 33.5 g

California

PHARMACEUTICALS

RX Only

Repackaged by California Pharmaceuticals, LLC, Camarillo, CA 93012

CS110-A1 rev 1

Ketophene Kit product label

NDC 70332-101-01

Rx only

RapidPaq™

Kit for Topical Cream

KETOPHENE™

(20% ketoprofen cream kit) Non-Steroid Anti-Inflammatory

Store kit at room temperature,

15-30°C (59-86°F0

Description:

This kit contains active and inactive materials to prepare approximately 167 grams of Ketoprofen topical cream. This kit may only be used for prescription compounding by an appropriate licensed medical professional, in response to a physician's prescription, to create a medication tailored to the specialized needs of an individual patient.

Active Ingredients:

- 33.5 g Ketoprofen, USP

Inactive Ingredients:

- 100 g RapidPaq Cream Base (D.l Water, Cetearyl Alcohol, Cyclomethicone, Polysorbate-60, Sorbitol, Phenoxyethanol (and) ethylhexylglycerin,

Tocopheryl Acetate, Aloe Barbadensis, Disodium EDTA)

- 33.5g ethoxy diglycol

- Spatula

- Instrustions

U. S. Patents Pending

Do not use if safety seal is broken

California

PHARMACEUTICALS

Repacked and Distributed By:

California Pharmaceuticals, LLC

768 Calle Plano

Camarillo, CA 93012

CS114-A1 rev 2